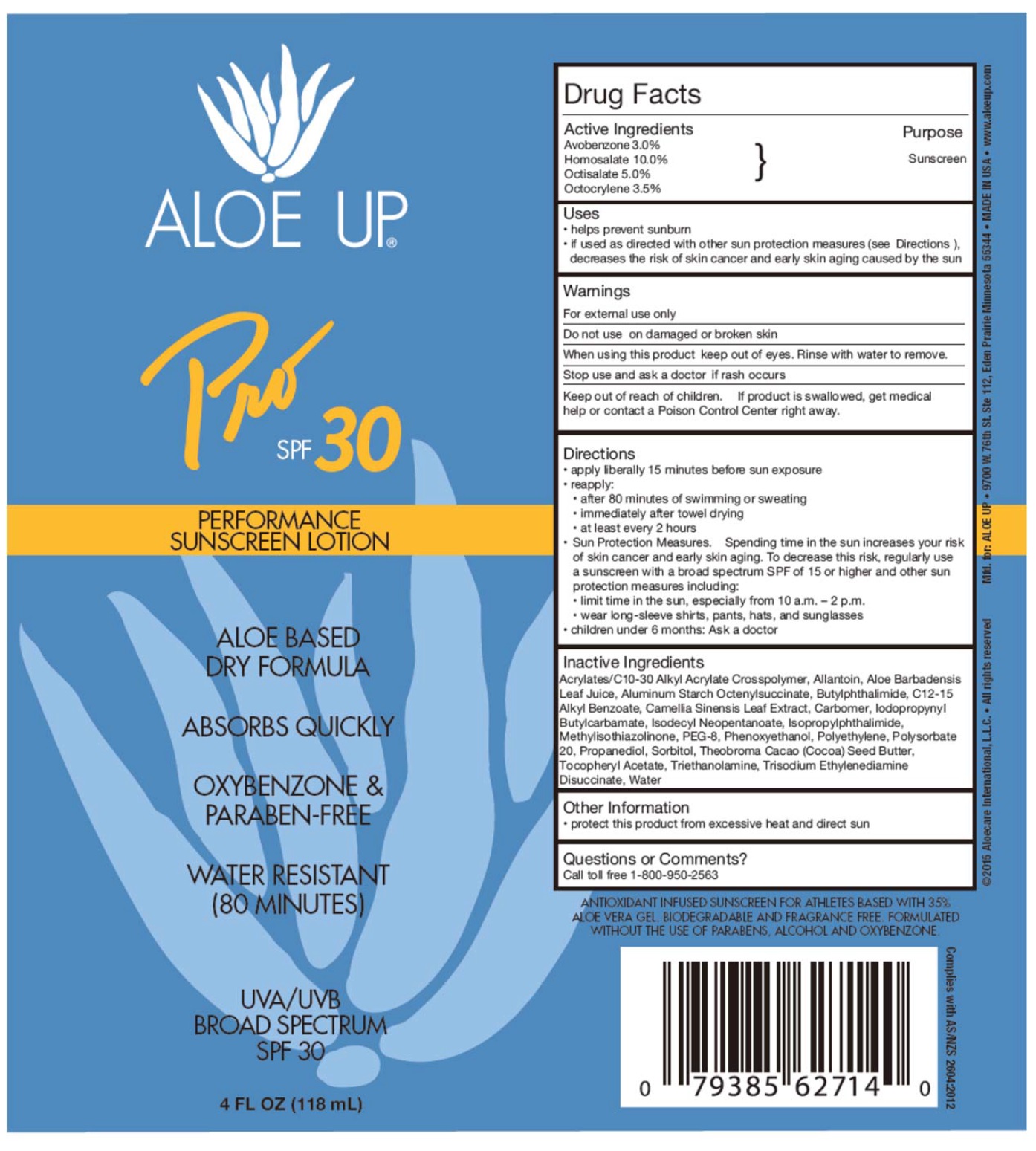 DRUG LABEL: Aloe Up
NDC: 58443-0230 | Form: LOTION
Manufacturer: Prime Enterprises Inc.
Category: otc | Type: HUMAN OTC DRUG LABEL
Date: 20200117

ACTIVE INGREDIENTS: AVOBENZONE 30 mg/1 mL; HOMOSALATE 100 mg/1 mL; OCTISALATE 50 mg/1 mL; OCTOCRYLENE 35 mg/1 mL
INACTIVE INGREDIENTS: GREEN TEA LEAF; IODOPROPYNYL BUTYLCARBAMATE; COCOA BUTTER; POLYETHYLENE GLYCOL 400; METHYLISOTHIAZOLINONE; ISOPROPYLPHTHALIMIDE; CARBOMER 940; ALLANTOIN; HIGH DENSITY POLYETHYLENE; POLYSORBATE 20; ISODECYL NEOPENTANOATE; SORBITOL; ALKYL (C12-15) BENZOATE; N-BUTYLPHTHALIMIDE; ALOE VERA LEAF; ALUMINUM STARCH OCTENYLSUCCINATE; (C10-C30)ALKYL METHACRYLATE ESTER; ALPHA-TOCOPHEROL ACETATE; TROLAMINE; WATER; PROPANEDIOL; PHENOXYETHANOL; TRISODIUM ETHYLENEDIAMINE DISUCCINATE

Aloe Up Pro SPF 30 Sunscreen Lotion

Active Ingredients

Avobenzone 3.0%

Homosalate 10.0%

Octisalate 5.0%

Octocrylene 3.5%

Purpose

Sunscreen

Uses

- helps prevent sunburn
- if used as directed with other sun protection measures (see Directions), decreases the risk of skin cancer and early skin aging caused by the sun

WARNINGS

For external use only.

Do not use on damaged or broken skin

When using this product keep out of eyes. Rinse with water to remove.

Stop use and ask a doctor if rash occurs

Keep out of reach of children. If product is swallowed, get medical help or contact a Poison Control Center right away.

Directions

- apply liberally 15 minutes before sun exposure
- reapply:
- after 80 minutes of swimming or sweating
- immediately after towel drying
- at least every 2 hours
- Sun Protection Measures. Spending time in the sun increases your risk of skin cancer and early skin aging. To decrease this risk, regularly use a sunscreen with broad spectrum SPF of 15 or higher and other sun protection measures including:
- limit time in the sun, especially from 10 a.m. – 2 p.m.
- wear long-sleeve shirts, pants, hats, and sunglasses
- children under 6 months: Ask a doctor

INACTIVE INGREDIENT

Acrylates/C10-30 Alkyl Acrylate Crosspolymer, Allantoin, Aloe Barbadensis Leaf Juice, Aluminum Starch Octenylsuccinate, Butylphthalimide, C12-15 Alkyl Benzoate, Camellia Sinensis (Green Tea) Leaf Extract, Carbomer, Iodopropynyl Butylcarbamate, Isodecyl Neopentanoate, Isopropylphthalimide, Methylisothiazolinone, PEG-8, Phenoxyethanol, Polyethylene, Polysorbate 20, Propanediol, Sorbitol, Theobroma Cacao (Cocoa) Seed Butter, Tocopheryl Acetate, Triethanolamine, Trisodium Ethylenediamine Disuccinate, Water

Other Information

- protect this product from excesive heat and direct sun

Questions or Comments?

Call toll free 1-800-950-2563